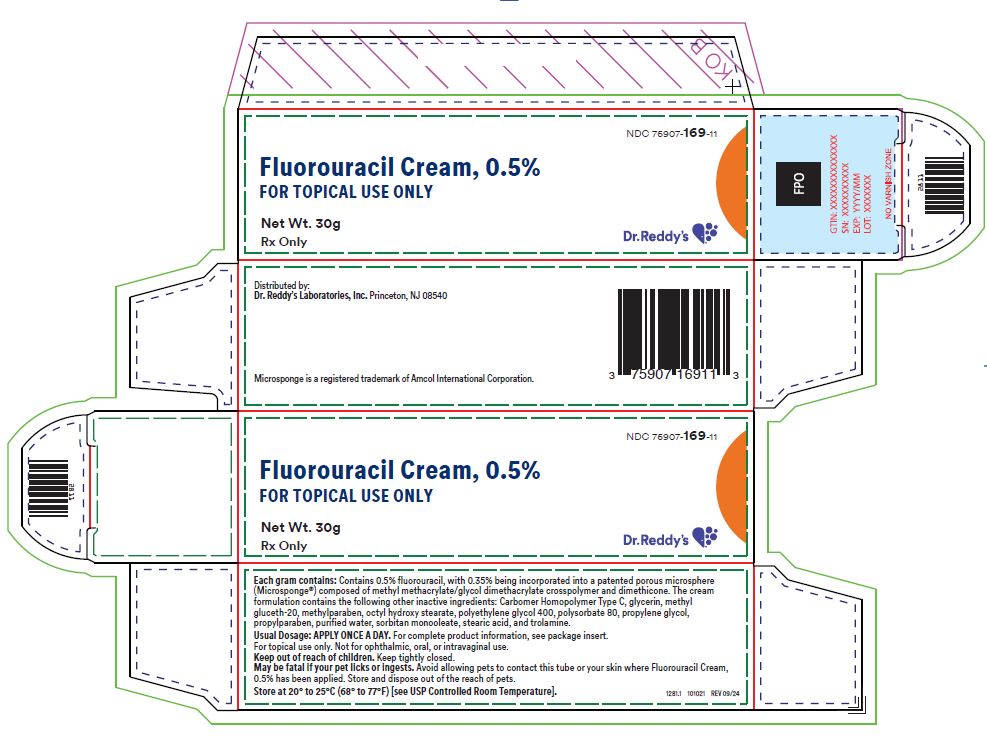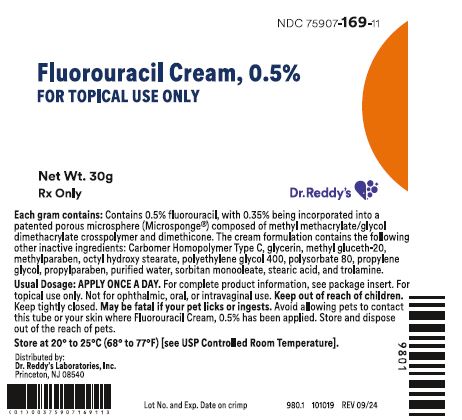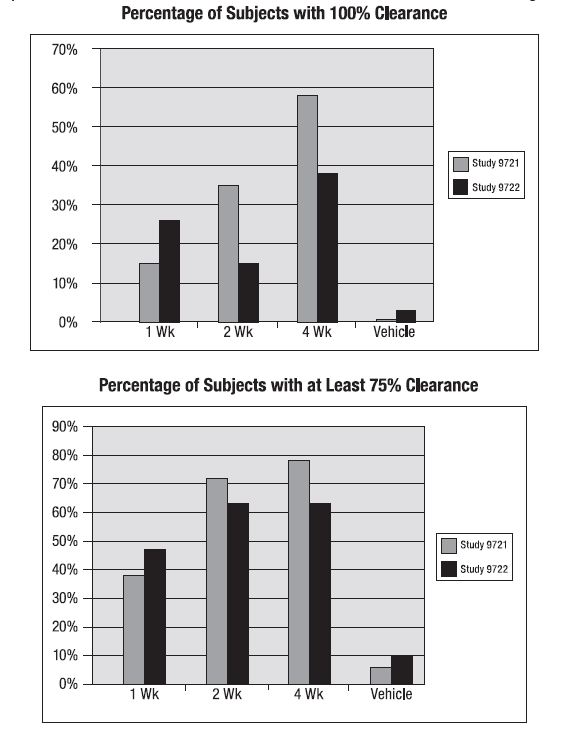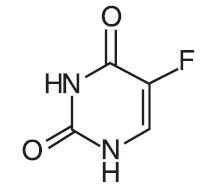 DRUG LABEL: FLUOROURACIL
NDC: 75907-169 | Form: CREAM
Manufacturer: Dr. Reddy's Laboratories Inc.
Category: prescription | Type: HUMAN PRESCRIPTION DRUG LABEL
Date: 20250711

ACTIVE INGREDIENTS: FLUOROURACIL 5 mg/1 g
INACTIVE INGREDIENTS: CARBOMER HOMOPOLYMER TYPE C; GLYCERIN; POLYETHYLENE GLYCOL 400; POLYSORBATE 80; SORBITAN MONOOLEATE; METHYL GLUCETH-20; STEARIC ACID; DIMETHICONE; TROLAMINE; PROPYLENE GLYCOL; METHYLPARABEN; PROPYLPARABEN; WATER; ETHYLHEXYL HYDROXYSTEARATE

Fluorouracil Cream, 0.5%
FOR TOPICAL DERMATOLOGIC USE ONLY
NOT FOR OPHTHALMIC, ORAL, OR INTRAVAGINAL USE

DESCRIPTION

Fluorouracil cream, 0.5%, contains fluorouracil for topical dermatologic use. Chemically, fluorouracil is 5-fluoro-2,4(1H, 3H)-pyrimidinedione. The molecular formula is C4H3FN2O2. Fluorouracil has a molecular weight of 130.08.

Fluorouracil cream contains 0.5% fluorouracil, with 0.35% being incorporated into a patented porous microsphere (Microsponge®) composed of methyl methacrylate/glycol dimethacrylate crosspolymer and dimethicone. The cream formulation contains the following other inactive ingredients: Carbomer Homopolymer Type C, glycerin, methyl gluceth-20, methylparaben, octyl hydroxy stearate, polyethylene glycol 400, polysorbate 80, propylene glycol, propylparaben, purified water, sorbitan monooleate, stearic acid, and trolamine.

CLINICAL PHARMACOLOGY

There is evidence that the metabolism of fluorouracil in the anabolic pathway blocks the methylation reaction of deoxyuridylic acid to thymidylic acid. In this manner, fluorouracil interferes with the synthesis of deoxyribonucleic acid (DNA) and to a lesser extent inhibits the formation of ribonucleic acid (RNA). Since DNA and RNA are essential for cell division and growth, the effect of fluorouracil may be to create a thymine deficiency that provokes unbalanced growth and death of the cell. The effects of DNA and RNA deprivation are most marked on those cells that grow more rapidly and take up fluorouracil at a more rapid rate. The contribution to efficacy or safety of individual components of the vehicle has not been established.

Pharmacokinetics:A multiple-dose, randomized, open-label, parallel study was performed in 21 patients with actinic keratoses. Twenty patients had pharmacokinetic samples collected: 10 patients treated with fluorouracil cream, 0.5% and 10 treated with Efudex® 5% Cream. Patients were treated for a maximum of 28 days with Fluorouracil cream, 0.5%, 1 g once daily in the morning; or Efudex® 5% Cream, 1 g twice daily, in the morning and evening. Steady-state plasma concentrations and the amounts of fluorouracil in urine resulting from the topical application of either product were measured. Three patients who received Fluorouracil cream, 0.5% and nine patients who received Efudex® 5% Cream had measurable plasma fluorouracil levels; however, only one patient receiving Fluorouracil cream, 0.5% and six patients receiving Efudex® 5% Cream had a sufficient number of data points to calculate mean pharmacokinetic parameters.

Plasma Pharmacokinetic Summary

PK Parameter | Fluorouracil Cream, 0.5% n=1 | Efudex® (Mean ± SD) n=6
Cmax | 0.77 ng/mL | 11.49 ± 8.24 ng/mL
Tmax | 1.00 hr | 1.03 ± 0.028 hr
AUC(0-24) | 2.80 ng•hr/mL | 22.39 ± 7.89 ng•hr/mL

Five of 10 patients receiving fluorouracil cream, 0.5% and nine of 10 patients receiving Efudex®5% Cream had measurable urine fluorouracil levels.

Urine Pharmacokinetic Summary

PK Parameter | Fluorouracil Cream, 0.5% (Mean ± SD) (Range) n=10 | Efudex® (Mean ± SD) (Range) n=10
Cum Ae† (min-max) | 2.74 ± 5.22 mcg (0-15.02) | 119.83 ± 94.80 mcg (0-329.87)
Max excretion rate (min-max) | 0.19 ± 0.52 mcg/hr (0-1.67) | 40.27 ± 47.14 mcg/hr (0-164.5)

†Cumulative urinary excretion

Both Fluorouracil cream, 0.5% and Efudex®5% Cream demonstrated low measurable plasma concentrations for fluorouracil when administered under steady-state conditions. Cumulative urinary excretion of fluorouracil was low for fluorouracil cream, 0.5% and for Efudex®, corresponding to 0.055% and 0.24% of the applied doses, respectively.

Clinical Trials:Under the experimental conditions of the topical safety studies, fluorouracil cream, 0.5% was not observed to cause contact sensitization. However, approximately 95% of subjects in the active arms of the Phase 3 clinical studies experienced facial irritation. Irritation is likely and sensitization is unlikely based on the results of the topical safety and Phase 3 studies.

Two Phase 3 identically designed, multicenter, vehicle-controlled, double-blind studies were conducted to evaluate the clinical safety and efficacy of fluorouracil cream, 0.5%. Patients with five or more actinic keratoses (AKs) on the face or anterior bald scalp were randomly allocated to active or vehicle treatment in a 2:1 ratio. Patients were randomly allocated to treatment durations of 1, 2, or 4 weeks in a 1:1:1 ratio. They applied the study cream once daily to the entire face/anterior bald scalp. Each patient’s clinical response was evaluated 4 weeks after the patient’s last scheduled application of study cream. No additional post-treatment follow-up efficacy or safety assessments were performed beyond 4 weeks after the last scheduled application. The following graphs show the percentage of patients in whom 100% of treated lesions cleared, and the percentage of patients in whom 75% or more of treated lesions cleared. Treatment with fluorouracil cream, 0.5% for 1, 2, or 4 weeks is compared to treatment with vehicle cream. Outcomes from 1, 2, and 4 weeks of treatment with vehicle cream are pooled because duration of treatment with vehicle had no substantive effect on clearance. Results from the two Phase 3 studies are shown separately. Although all treatment regimens of fluorouracil cream, 0.5% studied demonstrated efficacy over vehicle for the treatment of actinic keratosis, continuing treatment up to 4 weeks as tolerated results in further lesion reduction and clearing.

Clinical efficacy and safety in the treatment of AKs on the ears and other sun-exposed areas were not evaluated in the studies.

INDICATIONS AND USAGE

Fluorouracil cream, 0.5% is indicated for the topical treatment of multiple actinic or solar keratoses of the face and anterior scalp.

CONTRAINDICATIONS

Fluorouracil may cause fetal harm when administered to a pregnant woman. Fluorouracil is contraindicated in women who are or may become pregnant. If this drug is used during pregnancy, or if the patient becomes pregnant while taking this drug, the patient should be apprised of the potential hazard to the fetus.

No adequate and well-controlled studies have been conducted in pregnant women with either topical or parenteral forms of fluorouracil. One birth defect (ventricular septal defect) and cases of miscarriage have been reported when fluorouracil was applied to mucous membrane areas. Multiple birth defects have been reported in the fetus of a patient treated with intravenous fluorouracil.

Animal reproduction studies have not been conducted with fluorouracil cream, 0.5%. Fluorouracil, the active ingredient, has been shown to be teratogenic in mice, rats, and hamsters when administered parenterally at doses greater than or equal to 10, 15, and 33 mg/kg/day, respectively, [4X, 11X and 20X, respectively, the Maximum Recommended Human Dose (MRHD) based on body surface area (BSA)]. Fluorouracil was administered during the period of organogenesis for each species. Embryolethal effects occurred in monkeys at parenteral doses greater than 40 mg/kg/day (65X the MRHD based on BSA) administered during the period of organogenesis.

Fluorouracil cream, 0.5% should not be used in patients with dihydropyrimidine dehydrogenase (DPD) enzyme deficiency. A large percentage of fluorouracil is catabolized by the DPD enzyme. DPD enzyme deficiency can result in shunting of fluorouracil to the anabolic pathway, leading to cytotoxic activity and potential toxicities.

Fluorouracil cream, 0.5% is contraindicated in patients with known hypersensitivity to any of its components.

WARNINGS

The potential for a delayed hypersensitivity reaction to fluorouracil exists. Patch testing to prove hypersensitivity may be inconclusive.

Patients should discontinue therapy with fluorouracil cream, 0.5% if symptoms of DPD enzyme deficiency develop.

Rarely, unexpected systemic toxicity (e.g., stomatitis, diarrhea, neutropenia, neurotoxicity) associated with parenteral administration of fluorouracil has been attributed to deficiency of dihydropyrimidine dehydrogenase “DPD” activity. One case of life-threatening systemic toxicity has been reported with the topical use of 5% fluorouracil in a patient with a complete absence of DPD enzyme activity. Symptoms included severe abdominal pain, bloody diarrhea, vomiting, fever, and chills. Physical examination revealed stomatitis, erythematous skin rash, neutropenia, thrombocytopenia, inflammation of the esophagus, stomach, and small bowel. Although this case was observed with 5% fluorouracil cream, it is unknown whether patients with profound DPD enzyme deficiency would develop systemic toxicity with lower concentrations of topically applied fluorouracil.

Applications to mucous membranes should be avoided due to the possibility of local inflammation and ulceration.

PRECAUTIONS

General

There is a possibility of increased absorption through ulcerated or inflamed skin.

Information for the Patient

Patients using fluorouracil cream, 0.5% should receive the following information and instructions:

1. This medication is to be used as directed.
2. This medication should not be used for any disorder other than that for which it was prescribed.
3. It is for topical use only.
4. Avoid contact with the eyes, eyelids, nostrils, and mouth.
5. Cleanse affected area and wait 10 minutes before applying fluorouracil cream, 0.5%.
6. Wash hands immediately after applying fluorouracil cream, 0.5%.
7. Avoid prolonged exposure to sunlight or other forms of ultraviolet irradiation during treatment, as the intensity of the reaction may be increased.
8. Most patients using fluorouracil cream, 0.5% get skin reactions where the medicine is used. These reactions include redness, dryness, burning, pain, erosion (loss of the upper layer of skin), and swelling. Irritation at the application site may persist for two or more weeks after therapy is discontinued. Treated areas may be unsightly during and after therapy.
9. If you develop abdominal pain, bloody diarrhea, vomiting, fever, or chills while on fluorouracil cream, 0.5% therapy, stop the medication and contact your physician and/or pharmacist.
10. Report any side effects to the physician and/or pharmacist.
11. Fluorouracil, including fluorouracil cream, 0.5% may be fatal if ingested by pets. Avoid allowing pets to contact the fluorouracil cream, 0.5% container or the skin where fluorouracil cream, 0.5% has been applied. Store fluorouracil cream, 0.5% out of reach of pets. Safely discard or clean any cloth or applicator that may retain fluorouracil cream, 0.5% and avoid leaving any residues of fluorouracil cream, 0.5% on your hands, clothing, carpeting or furniture.

Laboratory Tests

To rule out the presence of a frank neoplasm, a biopsy may be considered for those areas failing to respond to treatment or recurring after treatment.

Carcinogenesis, Mutagenesis, Impairment of Fertility

Adequate long-term studies in animals to evaluate carcinogenic potential have not been conducted with fluorouracil. Studies with the active ingredient of fluorouracil cream, 0.5%, fluorouracil, have shown positive effects in in vitro and in vivo tests for mutagenicity and on impairment of fertility in in vivo animal studies.

Fluorouracil produced morphological transformation of cells in in vitro cell transformation assays. Morphological transformation was also produced in an in vitro assay by a metabolite of fluorouracil, and the transformed cells produced malignant tumors when injected into immunosuppressed syngeneic mice. Fluorouracil has been shown to exert mutagenic activity in yeast cells, Bacillus subtilis, and Drosophila assays. In addition, fluorouracil has produced chromosome damage at concentrations of 1.0 and 2.0 mcg/mL in an in vitro hamster fibroblast assay, was positive in a microwell mouse lymphoma assay, and was positive in in vivo micronucleus assays in rats and mice following intraperitoneal administration. Some patients receiving cumulative doses of 0.24 to 1.0 g of fluorouracil parenterally have shown an increase in numerical and structural chromosome aberrations in peripheral blood lymphocytes.

Fluorouracil has been shown to impair fertility after parenteral administration in rats. Fluorouracil administered at intraperitoneal doses of 125 and 250 mg/kg has been shown to induce chromosomal aberrations and changes in chromosome organization of spermatogonia in rats. In mice, single-dose intravenous and intraperitoneal injections of fluorouracil have been reported to kill differentiated spermatogonia and spermatocytes at a dose of 500 mg/kg and produce abnormalities in spermatids at 50 mg/kg.

Pediatric Use

Actinic keratosis is not a condition seen within the pediatric population, except in association with rare genetic diseases. Fluorouracil cream, 0.5% should not be used in children. The safety and effectiveness of fluorouracil cream, 0.5% have not been established in patients less than 18 years old.

Geriatric Use

No significant differences in safety and efficacy measures were demonstrated in patients age 65 and older compared to all other patients.

Pregnancy

See CONTRAINDICATIONS.

Nursing Women

It is not known whether fluorouracil is excreted in human milk. Because many drugs are excreted in human milk and because of the potential for serious adverse reactions in nursing infants from fluorouracil, a decision should be made whether to discontinue nursing or to discontinue the drug, taking into account the importance of the drug to the mother.

ADVERSE REACTIONS

The following were adverse events considered to be drug related and occurring with a frequency of 1% with fluorouracil cream, 0.5%: application site reaction (94.6%), and eye irritation (5.4%). The signs and symptoms of facial irritation (i.e., application site reaction) are presented below.

Summary of Facial Irritation Signs and Symptoms - Pooled Phase 3 Studies

Clinical Sign or Symptom | Active 1 Week N=85 | Active 2 Week N=87 | Active 4 Week N=85 | ALL Active Treatments N=257 | Vehicle Treatments N=127
 | n (%) | n (%) | n (%) | n (%) | n (%)
Erythema | 76 (89.4) | 82 (94.3) | 82 (96.5) | 240 (93.4) | 76 (59.8)
Dryness | 59 (69.4) | 76 (87.4) | 79 (92.9) | 214 (83.3) | 60 (47.2)
Burning | 51 (60.0) | 70 (80.5) | 71 (83.5) | 192 (74.7) | 28 (22.0)
Erosion | 21 (24.7) | 38 (43.7) | 54 (63.5) | 113 (44.0) | 17 (13.4)
Pain | 26 (30.6) | 34 (39.1) | 52 (61.2) | 112 (43.6) | 7 (5.5)
Edema | 12 (14.1) | 28 (32.2) | 51 (60.0) | 91 (35.4) | 6 (4.7)

During clinical trials, irritation generally began on Day 4 and persisted for the remainder of treatment. Severity of facial irritation at the last treatment visit was slightly below baseline for the vehicle group, mild to moderate for the 1-week active treatment group, and moderate for the 2- and 4-week active treatment groups. Mean severity declined rapidly for each active group after completion of treatment and was below baseline for each group at the Week 2 post-treatment follow-up visit.

Thirty-one patients (12% of those treated with fluorouracil cream, 0.5% in the Phase 3 clinical studies) discontinued study treatment early due to facial irritation. Except for three patients, discontinuation of treatment occurred on or after Day 11 of treatment.

Eye irritation adverse events, described as mild to moderate in intensity, were characterized as burning, watering, sensitivity, stinging, and itching. These adverse events occurred across all treatment arms in one of the two Phase 3 studies.

Summary of All Adverse Events Reported in ≥ 1% of Patients in the Combined Active Treatment and Vehicle Groups – Pooled Phase 3 Studies

9721 and 9722 Combined
Adverse Event | Active 1 Week N=85 | Active 2 Week N=87 | Active 4 Week N=85 | ALL Active Treatments N=257 | Vehicle Treatments N=127
 | n (%) | n (%) | n (%) | n (%) | n (%)
BODY AS A WHOLE Headache Allergy Infection Upper Respiratory | 7 (8.2) 3 (3.5) 4 (4.7) 0 0 | 6 (6.9) 2 (2.3) 0 2 (2.3) 0 | 12 (14.1) 3 (3.5) 2 (2.4) 1 (1.2) 0 | 25 (9.7) 8 (3.1) 6 (2.3) 3 (1.2) 0 | 15 (11.8) 3 (2.4) 3 (2.4) 2 (1.6) 2 (1.6)
MUSCULOSKELETAL Muscle Soreness | 1 (1.2) 0 | 1 (1.1) 0 | 1 (1.2) 0 | 3 (1.2) 0 | 5 (3.9) 2 (1.6)
RESPIRATORY Sinusitis | 5 (5.9) 4 (4.7) | 0 0 | 1 (1.2) 0 | 6 (2.3) 4 (1.6) | 6 (4.7) 2 (1.6)
SKIN & APPENDAGES Application site Reaction Irritation Skin | 78 (91.8) 78 (91.8) 1 (1.2) | 83 (95.4) 83 (95.4) 0 | 82 (96.5) 82 (96.5) 2 (2.4) | 243 (94.6) 243 (94.6) 3 (1.2) | 85 (66.9) 83 (65.4) 0
SPECIAL SENSES Eye Irritation | 6 (7.1) 5 (5.9) | 4 (4.6) 3 (3.4) | 6 (7.1) 6 (7.1) | 16 (6.2) 14 (5.4) | 6 (4.7) 3 (2.4)

Adverse Experiences Reported by Body System:In the Phase 3 studies, no serious adverse event was considered related to study drug. A total of five patients, three in the active treatment groups and two in the vehicle group, experienced at least one serious adverse event. Three patients died as a result of adverse event(s) considered unrelated to study drug (stomach cancer, myocardial infarction, and cardiac failure).

Post-treatment clinical laboratory tests other than pregnancy tests were not performed during the Phase 3 clinical studies. Clinical laboratory tests were performed during conduct of a Phase 2 study of 104 patients and 21 patients in a Phase 1 study. No abnormal serum chemistry, hematology, or urinalysis results in these studies were considered clinically significant.

To report SUSPECTED ADVERSE EVENTS, contact Dr. Reddy’s Laboratories Inc, at 1-888-375-3784 or FDA at 1-800-FDA-1088 or http://www.fda.gov/medwatch for voluntary reporting of adverse reactions.

DOSAGE AND ADMINISTRATION

Fluorouracil cream, 0.5% should be applied once a day to the skin where actinic keratosis lesions appear, using enough to cover the entire area with a thin film. Fluorouracil cream, 0.5% should not be applied near the eyes, nostrils, or mouth. Fluorouracil cream, 0.5% should be applied 10 minutes after thoroughly washing, rinsing, and drying the entire area. Fluorouracil cream, 0.5% may be applied using the fingertips. Immediately after application, the hands should be thoroughly washed. Fluorouracil cream, 0.5% should be applied up to 4 weeks as tolerated. Continued treatment up to 4 weeks results in greater lesion reduction. Local irritation is not markedly increased by extending treatment from 2 to 4 weeks, and is generally resolved within 2 weeks of cessation of treatment.

OVERDOSE

Ordinarily, topical overdosage will not cause acute problems. If Fluorouracil cream, 0.5% is accidentally ingested, induce emesis and gastric lavage. Administer symptomatic and supportive care as needed.

If contact is made with the eye, flush with copious amounts of water.

HOW SUPPLIED

Fluorouracil Cream, 0.5%, is a white to off-white cream, supplied as follows: NDC 75907-169-11: 30 g tube
Store at 20°C to 25°C (68°F to 77°F) [see USP Controlled Room Temperature].

Keep out of reach of children.
Rx Only

Distributed by: Dr. Reddy’s Laboratories, Inc.
Princeton, NJ 08540 U.S .A.

Revised: 07/2025
101042

Microsponge is a registered trademark of Amcol International Corporation. Efudex is a trademark of Bausch Health Companies Inc. or its affiliates. All other product/brand names are trademarks of their respective owners.

PATIENT INFORMATION

Fluorouracil Cream, 0.5%

Read this leaflet carefully before you start to use your medicine. Read the information you get every time you get more medicine. There may be new information about the drug. This leaflet does not take the place of talks with your doctor. If you have any questions or are not sure about something, ask your doctor or pharmacist.

What is fluorouracil cream, 0.5%?
Fluorouracil cream, 0.5% is a cream used by adults to treat skin conditions on the face and front part of the scalp called solar keratosis or actinic keratosis.

Who should not use fluorouracil cream, 0.5%?
Do not use fluorouracil cream, 0.5%:

- if you are pregnant or might become pregnant. Fluorouracil cream, 0.5% may harm your unborn child.
- if you are nursing a baby. We do not know if fluorouracil cream, 0.5% can pass to the baby through the milk.
- if you have dihydropyrimidine dehydrogenase (DPD) enzyme deficiency. The active ingredient in fluorouracil cream, 0.5%, fluorouracil, can cause serious side effects in patients who are DPD enzyme deficient. If you have DPD enzyme deficiency and use medications containing fluorouracil, you may develop serious side effects such as stomach pain, bloody diarrhea, vomiting, fever, or chills.
- if you are allergic to the ingredients in fluorouracil cream, 0.5%. Ask your doctor or pharmacist about the inactive ingredients.
- if you are under 18 years of age. Fluorouracil cream, 0.5% should not be used in children.

Tell your doctor if you are able to become pregnant. Your doctor may advise you about birth control to avoid pregnancy.

How should I use fluorouracil cream, 0.5%?
Use fluorouracil cream, 0.5% once a day as instructed by your doctor. Use it only on your skin. You should use fluorouracil cream, 0.5% for up to 4 weeks.
1. Clean the area where you will apply fluorouracil cream, 0.5%. Rinse well and dry the area with a towel and wait 10 minutes before applying fluorouracil cream, 0.5%.
2. Put fluorouracil cream, 0.5% on your face as directed by your physician, using your fingertips. Use enough to cover the affected skin.
3. Avoid contact with your eyes, nostrils, and mouth.
4. Wash your hands as soon as you finish putting fluorouracil cream, 0.5% on your skin.
5. A moisturizer/sunscreen may be applied 2 hours after fluorouracil cream, 0.5% has been applied. Do not use any other skin products, including creams, lotions, medications, or cosmetics – unless instructed by your doctor.

What should I avoid while using fluorouracil cream, 0.5%?
Avoid sunlight or other ultraviolet light (such as tanning booths) as much as possible while using fluorouracil cream, 0.5%. Sunlight may increase your side effects. When exposed to sunlight, wear a hat and use sunscreen.

Do not cover the treated skin with a dressing.

Do not breast feed or become pregnant while using fluorouracil cream, 0.5%. If you do become pregnant, stop using fluorouracil cream, 0.5% and tell your doctor right away.

Fluorouracil cream, 0.5% may be fatal to your pet if your pet licks or ingests fluorouracil cream, 0.5%.

- Avoid allowing pets to contact the fluorouracil cream, 0.5% container or your skin where you applied fluorouracil cream, 0.5%.
- Store fluorouracil cream, 0.5% out of reach of pets.
- Safely discard or clean any cloth or applicator that may have fluorouracil cream, 0.5% residue.
- Avoid applying fluorouracil cream, 0.5% on your clothing, carpeting, or furniture.
- If your pet starts vomiting or starts having a seizure after your pet licks or ingests fluorouracil cream, 0.5%, seek immediate veterinary care for your pet.

What are the possible side effects of fluorouracil cream, 0.5%?
Most patients using fluorouracil cream, 0.5% get skin reactions where the medicine is used. These reactions include redness, dryness, burning, pain, erosion (loss of the upper layer of skin), and swelling. Irritation may continue for 2 or more weeks after treatment is over. The treated area may become unsightly during therapy.

Some patients get eye irritation. Eye irritation might consist of burning, sensitivity, itching, stinging, and watering. If you are concerned about side effects, talk to your doctor.

A few patients have reported side effects such as stomach pain, diarrhea, vomiting, fever, or chills, possibly due to the lack of a specific enzyme, DPD, in their body. If you experience any of these symptoms, discontinue therapy immediately, and contact your doctor.

Storage information
Keep this medicine at room temperature 68°F to 77°F (20°C to 25°C). Throw away unused medicine. Keep this medicine out of reach of children.

General advice about prescription medicines
Medicines are sometimes prescribed for conditions that are not described in patient information leaflets. Do not use fluorouracil cream, 0.5% for a condition for which it was not prescribed. This medicine is for your use only. Never give it to other people. It may harm them even if their skin problem appears to be the same as yours. Do not use fluorouracil cream, 0.5% after the expiration date on the tube.

Distributed by:
Dr. Reddy’s Laboratories, Inc.
Princeton, NJ 08540 U.S.A.

PACKAGE LABEL PRINCIPAL DISPLAY PANEL SECTION

Fluorouracil cream, 0.5% Carton Label
NDC 75907-169-11

Container label